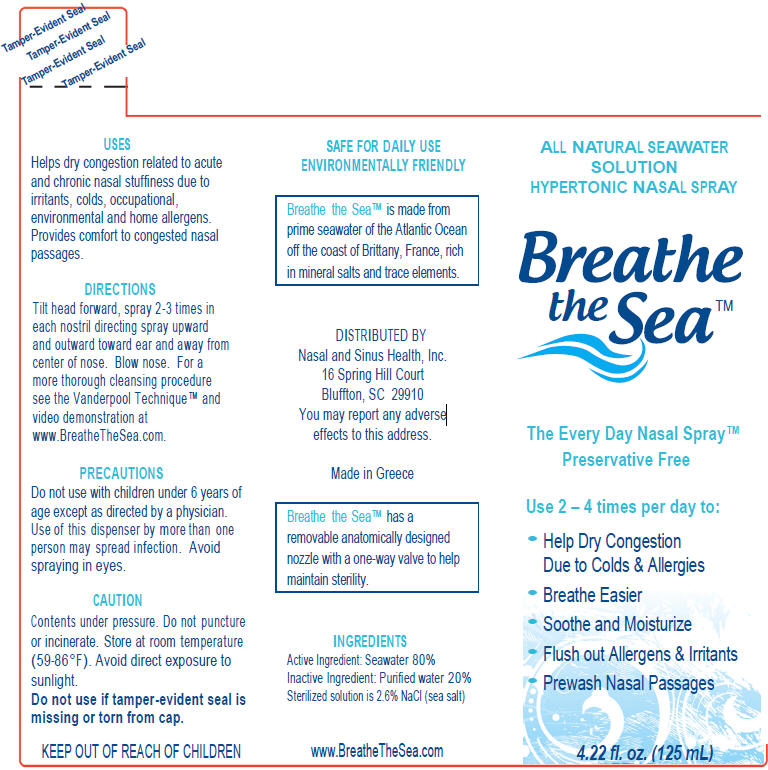 DRUG LABEL: Breathe the Sea 
NDC: 52429-124 | Form: SPRAY
Manufacturer: Nasal and Sinus Health, Inc.
Category: otc | Type: HUMAN OTC DRUG LABEL
Date: 20120217

ACTIVE INGREDIENTS: Sodium Chloride 2600 mg/100 mL
INACTIVE INGREDIENTS: water

Breathe the Sea™ All-Natural Seawater Solution
Hypertonic Nasal Spray

PURPOSE

USES

Helps dry congestion related to acute and chronic nasal stuffiness due to irritants, colds, occupational, environmental and home allergens. Provides comfort to congested nasal passages.

DIRECTIONS

Tilt head forward, spray 2-3 times in each nostril directing spray upward and outward toward ear and away from center of nose. Blow nose. For a more thorough cleansing procedure see the Vanderpool Technique ™ and video demonstration at www.BreatheTheSea.com.

PRECAUTIONS

Do not use with children under 6 years of age except as directed by a physician.

WHEN USING

Use of this dispenser by more than one person may spread infection. Avoid spraying in eyes.

CAUTION

Contents under pressure. Do not puncture or incinerate. Store at room temperature (59-86°F). Avoid direct exposure to sunlight.

Do not use if tamper-evident seal is missing or torn from cap.

KEEP OUT OF REACH OF CHILDREN

DISTRIBUTED BY
Nasal and Sinus Health, Inc.
16 Spring Hill Court
Bluffton, SC 29910

You may report any adverse effects to this address.

INGREDIENTS

Active Ingredient: Seawater 80%

Inactive Ingredient: Purified water 20% Sterilized solution is 2.6% NaCl (sea salt)

PRINCIPAL DISPLAY PANEL - 125 mL Canister Label

ALL NATURAL SEAWATER
SOLUTION
HYPERTONIC NASAL SPRAY

Breathe
the Sea™

The Every Day Nasal Spray™
Preservative Free

Use 2 – 4 times per day to:

- Help Dry Congestion
  Due to Colds & Allergies
- Breathe Easier
- Soothe and Moisturize
- Flush out Allergens & Irritants
- Prewash Nasal Passages

4.22 fl. oz. (125 mL)